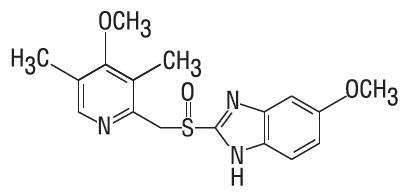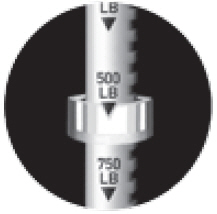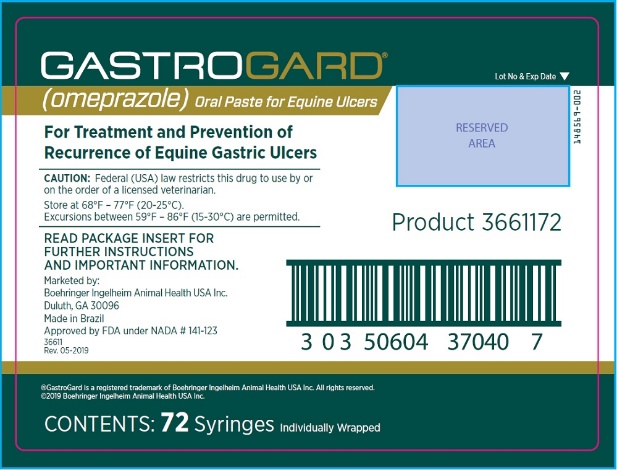 DRUG LABEL: GASTROGARD
NDC: 0010-3704 | Form: PASTE
Manufacturer: Boehringer Ingelheim Animal Health USA Inc.
Category: animal | Type: PRESCRIPTION ANIMAL DRUG LABEL
Date: 20200811

ACTIVE INGREDIENTS: omeprazole 370 mg/1 g

GASTROGARD®
(omeprazole) Oral Paste for Equine Ulcers

Oral Paste for Horses and Foals

Approved by FDA under NADA # 141-123

Caution

Federal (USA) law restricts this drug to use by or on the order of a licensed veterinarian.

Description

Chemical name: 5-Methoxy-2-[[(4-methoxy-3,5-dimethyl-2-pyridinyl) methyl] sulfinyl]-1H-benzimidazole. Empirical formula: C17H19N3O3S. Molecular weight: 345.42. Structural formula:

How Supplied

GastroGard (omeprazole) Paste for horses contains 37% w/w omeprazole and is available in an adjustable-dose syringe. Each syringe contains 2.28 g of omeprazole. Syringes are calibrated according to body weight and are available in boxes of 7 units or 72 units.

Storage Conditions

Store at 68°F – 77°F (20-25°C). Excursions between 59°F – 86°F (15-30°C) are permitted.

Indications

For treatment and prevention of recurrence of gastric ulcers in horses and foals 4 weeks of age and older.

Dosage Regimen

For treatment of gastric ulcers, GastroGard Paste should be administered orally once-a-day for 4 weeks at the recommended dosage of 1.8 mg omeprazole/lb body weight (4 mg/kg). For the prevention of recurrence of gastric ulcers, continue treatment for at least an additional 4 weeks by administering GastroGard Paste at the recommended daily maintenance dose of 0.9 mg/lb (2 mg/kg).

Directions For Use

GastroGard Paste for horses is recommended for use in horses and foals 4 weeks of age and older. The contents of one syringe will dose a 1250 lb (568 kg) horse at the rate of 1.8 mg omeprazole/lb body weight (4 mg/kg). For treatment of gastric ulcers, each weight marking on the syringe plunger will deliver sufficient omeprazole to treat 250 lb (114 kg) body weight. For prevention of recurrence of gastric ulcers, each weight marking will deliver sufficient omeprazole to dose 500 lb (227 kg) body weight.

To deliver GastroGard Paste at the treatment dose rate of 1.8 mg omeprazole/lb body weight (4 mg/kg), set the syringe plunger to the appropriate weight marking according to the horse's weight in pounds.

To deliver GastroGard Paste at the dose rate of 0.9 mg/lb (2 mg/kg) to prevent recurrence of ulcers, set the syringe plunger to the weight marking corresponding to half of the horse's weight in pounds.

To set the syringe plunger:
1) While holding plunger, turn the knurled ring on the plunger ¼ turn to the left and slide the knurled ring along the plunger shaft so that the side nearest the barrel is at the appropriate weight marking, aligning the arrow on the plunger with the notch on the ring, as shown in the pictogram.
2) Lock the ring in place by making ¼ turn to the right. Ensure it is locked (it should no longer slide).

Make sure the horse's mouth contains no feed. Remove the cover from the tip of the syringe, and insert the syringe into the horse's mouth at the interdental space. Depress the plunger until stopped by the knurled ring. The dose should be deposited on the back of the tongue or deep into the cheek pouch. Care should be taken to ensure that the horse consumes the complete dose. Treated animals should be observed briefly after administration to ensure that part of the dose is not lost or rejected. If any of the dose is lost, redosing is recommended.

If, after dosing, the syringe is not completely empty, it may be reused on following days until emptied. Replace the cap after each use.

Warning

Do not use in horses intended for human consumption. Keep this and all drugs out of the reach of children. In case of ingestion, contact a physician. Physicians may contact a poison control center for advice concerning accidental ingestion.

Adverse Reactions

In efficacy trials, when the drug was administered at 1.8 mg omeprazole/lb (4 mg/kg) body weight daily for 28 days and 0.9 mg omeprazole/lb (2 mg/kg) body weight daily for 30 additional days, no adverse reactions were observed.

To report suspected adverse drug events, for technical assistance, or to obtain a copy of the Safety Data Sheet (SDS), contact Boehringer Ingelheim Animal Health USA Inc. at 1-888-637-4251. For additional information about adverse drug experience reporting for animal drugs, contact FDA at 1-888-FDA-VETS, or online at www.fda.gov/reportanimalae.

Precautions

The safety of GastroGard Paste has not been determined in pregnant or lactating mares.

Clinical Pharmacology

Mechanism of Action: Omeprazole is a gastric acid pump inhibitor that regulates the final step in hydrogen ion production and blocks gastric acid secretion regardless of the stimulus. Omeprazole irreversibly binds to the gastric parietal cell's H+, K+ ATPase enzyme which pumps hydrogen ions into the lumen of the stomach in exchange for potassium ions. Since omeprazole accumulates in the cell cannaliculi and is irreversibly bound to the effect site, the plasma concentration at steady state is not directly related to the amount that is bound to the enzyme. The relationship between omeprazole action and plasma concentration is a function of the rate-limiting process of H+, K+ ATPase activity/turnover. Once all of the enzyme becomes bound, acid secretion resumes only after new H+, K+ ATPase is synthesized in the parietal cell (i.e., the rate of new enzyme synthesis exceeds the rate of inhibition).

Pharmacodynamics: In a study of pharmacodynamic effects using horses with gastric cannulae, secretion of gastric acid was inhibited in horses given 4 mg omeprazole/kg/day. After the expected maximum suppression of gastric acid secretion was reached (5 days), the actual secretion of gastric acid was reduced by 99%, 95% and 90% at 8, 16, and 24 hours, respectively.

Pharmacokinetics: In a pharmacokinetic study involving thirteen healthy, mixed breed horses (8 female, 5 male) receiving multiple doses of omeprazole paste (1.8 mg/lb once daily for fifteen days) in either a fed or fasted state, there was no evidence of drug accumulation in the plasma when comparing the extent of systemic exposure (AUC0-∞). When comparing the individual bioavailability data (AUC0-∞ , Cmax, and Tmax measurements) across the study days, there was great inter- and intrasubject variability in the rate and extent of product absorption. Also, the extent of omeprazole absorption in horses was reduced by approximately 67% in the presence of food. This is evidenced by the observation that the mean AUC0-∞ values measured during the fifth day of omeprazole therapy when the animals were fasted for 24 hours was approximately three times greater than the AUC estimated after the first and fifteenth doses when the horses were fed hay ad libitum and sweet feed (grain) twice daily. Prandial status did not affect the rate of drug elimination. The terminal half-life estimates (N=38) ranged from approximately one-half to eight hours.

Efficacy

Dose Confirmation: GastroGard (omeprazole) Paste, administered to provide omeprazole at 1.8 mg/lb (4 mg/kg) daily for 28 days, effectively healed or reduced the severity of gastric ulcers in 92% of omeprazole-treated horses. In comparison, 32% of controls exhibited healed or less severe ulcers. Horses enrolled in this study were healthy animals confirmed to have gastric ulcers by gastroscopy. Subsequent daily administration of GastroGard Paste to provide omeprazole at 0.9 mg/lb (2 mg/kg) for 30 days prevented recurrence of gastric ulcers in 84% of treated horses, whereas ulcers recurred or became more severe in horses removed from omeprazole treatment.

Clinical Field Trials: GastroGard Paste administered at 1.8 mg/lb (4 mg/kg) daily for 28 days healed or reduced the severity of gastric ulcers in 99% of omeprazole-treated horses. In comparison, 32.4% of control horses had healed ulcers or ulcers which were reduced in severity. These trials included horses of various breeds and under different management conditions, and included horses in race or show training, pleasure horses, and foals as young as one month. Horses enrolled in the efficacy trials were healthy animals confirmed to have gastric ulcers by gastroscopy. In these field trials, horses readily accepted GastroGard Paste. There were no drug related adverse reactions. In the clinical trials, GastroGard Paste was used concomitantly with other therapies, which included: anthelmintics, antibiotics, non-steroidal and steroidal anti-inflammatory agents, diuretics, tranquilizers and vaccines.

Diagnostic and Management Considerations: The following clinical signs may be associated with gastric ulceration in adult horses: inappetance or decreased appetite, recurrent colic, intermittent loose stools or chronic diarrhea, poor hair coat, poor body condition, or poor performance. Clinical signs in foals may include: bruxism (grinding of teeth), excessive salivation, colic, cranial abdominal tenderness, anorexia, diarrhea, sternal recumbency or weakness. A more accurate diagnosis of gastric ulceration in horses and foals may be made if ulcers are visualized directly by endoscopic examination of the gastric mucosa. Gastric ulcers may recur in horses if therapy to prevent recurrence is not administered after the initial treatment is completed. Use GastroGard Paste at 0.9 mg omeprazole/lb body weight (2 mg/kg) for control of gastric ulcers following treatment. The safety of administration of GastroGard Paste for longer than 91 days has not been determined. Maximal acid suppression occurs after three to five days of treatment with omeprazole.

Safety

GastroGard Paste was well tolerated in the following controlled efficacy and safety studies.

In field trials involving 139 horses, including foals as young as one month of age, no adverse reactions attributable to omeprazole treatment were noted.

In a placebo controlled adult horse safety study, horses received 20 mg/kg/day omeprazole (5x the recommended dose) for 90 days. No treatment related adverse effects were observed.

In a placebo controlled tolerance study, adult horses were treated with GastroGard Paste at a dosage of 40 mg/kg/day (10x the recommended dose) for 21 days. No treatment related adverse effects were observed.

A placebo controlled foal safety study evaluated the safety of omeprazole at doses of 4, 12 or 20 mg/kg (1, 3 or 5x) once daily for 91 days. Foals ranged in age from 66 to 110 days at study initiation. Gamma glutamyltransferase (GGT) levels were significantly elevated in horses treated at exaggerated doses of 20 mg/kg (5x the recommended dose). Mean stomach to body weight ratio was higher for foals in the 3x and 5x groups than for controls; however, no abnormalities of the stomach were evident on histological examination.

Reproductive Safety

In a male reproductive safety study, 10 stallions received GastroGard Paste at 12 mg/kg/day (3x the recommended dose) for 70 days. No treatment related adverse effects on semen quality or breeding behavior were observed. A safety study in breeding mares has not been conducted.

Marketed by:
Boehringer Ingelheim Animal Health USA Inc.
Duluth, GA 30096
Made in Brazil

®GastroGard is a registered trademark of Boehringer Ingelheim Animal Health USA Inc. All rights reserved.
©2019 Boehringer Ingelheim Animal Health USA Inc.

Rev. 05-2019

Principal Display Panel – 72 syringe box label

GASTROGARD®
(omeprazole) Oral Paste for Equine Ulcers

For Treatment and Prevention of
Recurrence of Equine Gastric Ulcers

CAUTION: Federal (USA) law restricts this drug to use by or on the order of a licensed veterinarian.

Store at 68°F – 77°F (20-25°C). Excursions between 59°F – 86°F (15-30°C) are permitted.

READ PACKAGE INSERT FOR
FURTHER INSTRUCTIONS
AND IMPORTANT INFORMATION.

Marketed by:
Boehringer Ingelheim Animal Health USA Inc.
Duluth, GA 30096
Made in Brazil

Approved by FDA under NADA # 141-123

®GastroGard is a registered trademark of Boehringer Ingelheim Animal Health USA Inc. All rights reserved.
©2019 Boehringer Ingelheim Animal Health USA Inc.

CONTENTS: 72 Syringes Individually Wrapped